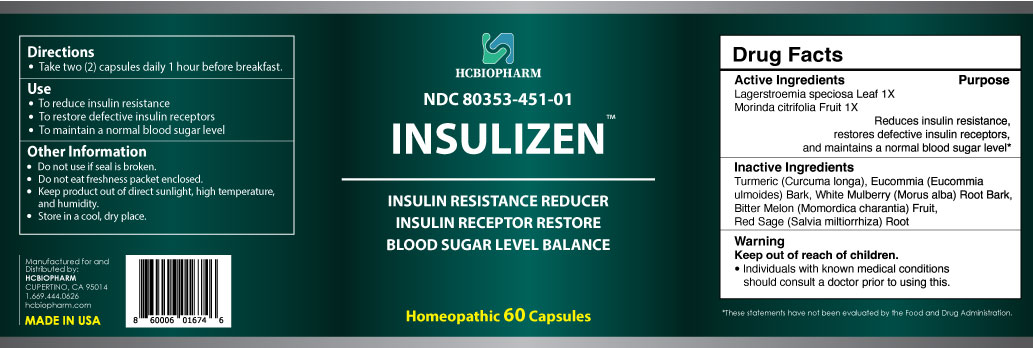 DRUG LABEL: Insulizen
NDC: 80353-451 | Form: CAPSULE
Manufacturer: HCBIOPHARM LLC
Category: homeopathic | Type: HUMAN OTC DRUG LABEL
Date: 20250103

ACTIVE INGREDIENTS: LAGERSTROEMIA SPECIOSA LEAF 1 [hp_X]/1 1; MORINDA CITRIFOLIA FRUIT 1 [hp_X]/1 1
INACTIVE INGREDIENTS: CURCUMA LONGA WHOLE; EUCOMMIA ULMOIDES BARK; MORUS ALBA ROOT BARK; MOMORDICA CHARANTIA FRUIT; SALVIA MILTIORRHIZA ROOT

Active Ingredients

Lagerstroemia speciosa Leaf 1X, Morinda citrifolia Fruit 1X

Purpose

Reduces insulin resistance, restores defective insulin receptors, and maintains a normal blood sugar level*

Keep Out of Reach of Children

Directions

Take two (2) capsules daily 1 hour before breakfast.

Use

- To reduce insulin resistance
- To restore defective insulin receptors
- To maintain a normal blood sugar level

Inactive Ingredients

Turmeric (Curcuma longa), Eucommia (Eucommia ulmoides) Bark, White Mulberry (Morus alba) Root Bark, Bitter Melon (Momordica charantia) Fruit, Red Sage (Salvia miltiorrhiza) Root

Warning

Individuals with known medical conditions should consult a doctor prior to using this.

Other Information

Do not use if seal is broken.
Do not eat freshness packet enclosed.
Keep product out of direct sunlight, high temperature, and humidity.
Store in a cool, dry place.

Package Label Display

Insulizen

INSULIN RESISTANCE REDUCER
INSULIN RECEPTOR RESTORE
BLOOD SUGAR LEVEL BALANCE

Homeopathic 60 Capsules